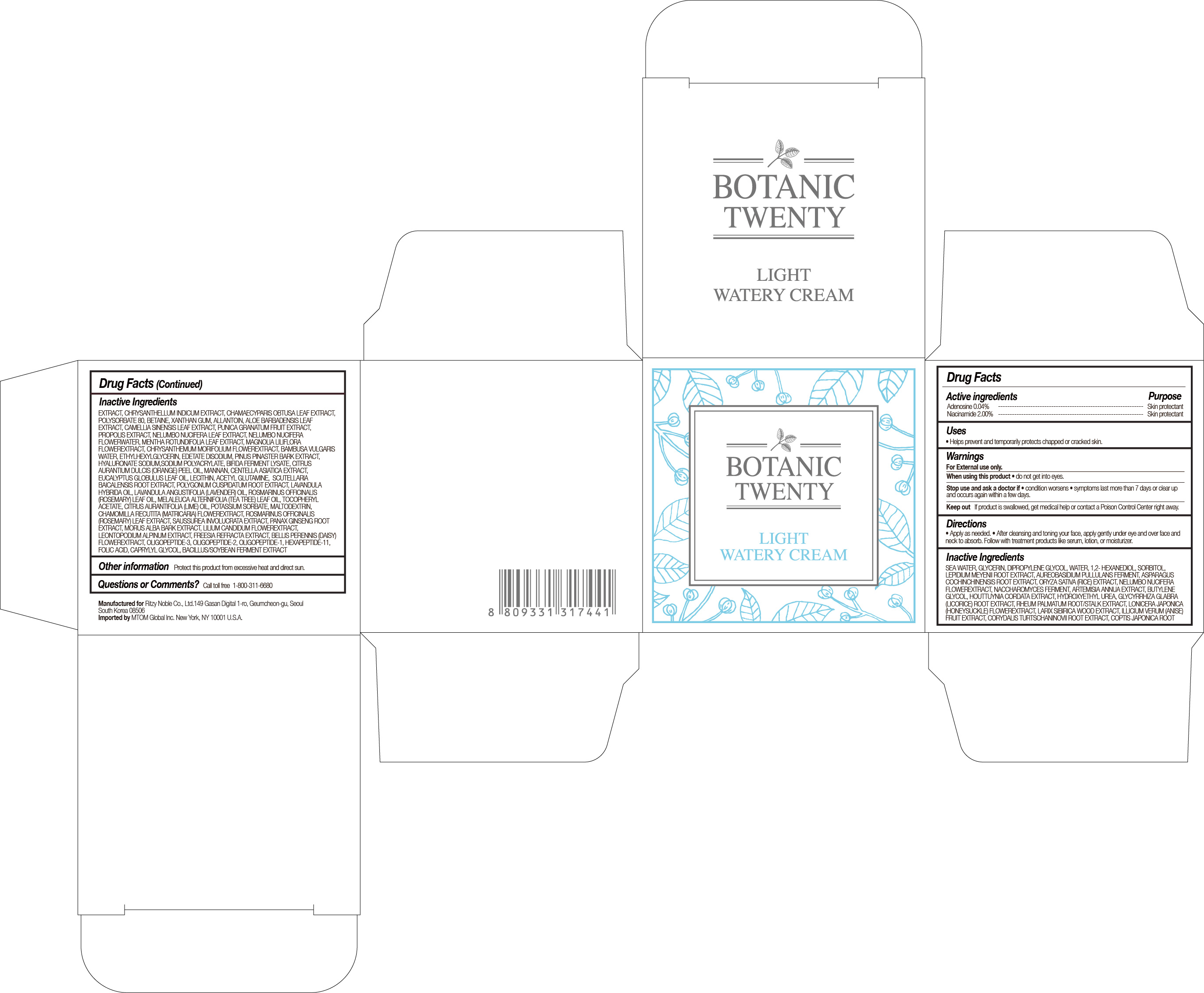 DRUG LABEL: BOTANIC TWENTY
NDC: 71364-003 | Form: CREAM
Manufacturer: RITZY NOBLE CO., LTD.
Category: otc | Type: HUMAN OTC DRUG LABEL
Date: 20180101

ACTIVE INGREDIENTS: ADENOSINE 0.04 g/50 mL; NIACINAMIDE 2 g/50 mL
INACTIVE INGREDIENTS: 1,2-HEXANEDIOL; DIPROPYLENE GLYCOL; NELUMBO NUCIFERA FLOWER; ARTEMISIA ANNUA WHOLE; SACCHAROMYCES LYSATE; COPTIS JAPONICA ROOT; CHAMAECYPARIS OBTUSA LEAF; RHEUM PALMATUM ROOT; BUTYLENE GLYCOL; LEPIDIUM MEYENII ROOT; AUREOBASIDIUM PULLULANS VAR. PULLUTANS; WATER; GLYCERIN; LONICERA JAPONICA FLOWER; CHRYSANTHEMUM INDICUM FLOWER; CORYDALIS TURTSCHANINOVII WHOLE; ILLICIUM VERUM WHOLE; LARIX SIBIRICA WOOD; ASPARAGUS COCHINCHINENSIS WHOLE; HOUTTUYNIA CORDATA TOP; ORYZA SATIVA WHOLE; GLYCYRRHIZA GLABRA; CETEARYL ETHYLHEXANOATE

Botanic Twenty Light Watery Cream

BOTANIC TWENTY LIGHT WATERY CREAM

ACTIVE INGREDIENTS

ADENOSINE 0.04%

NIACINAMIDE 2.00%

PURPOSE

SKIN PROTECTANT

USES

Helps prevent and temporarily protects chapped or cracked skin.

WARNINGS

FOR EXTERNAL USE ONLY

WHEN USING THIS PRODUCT

• do not get into eyes.

STOP USE AND ASK A DOCTOR IF

• condition worsens

• symptoms last more than 7 days or clear up and occurs again within a few days.

KEEP OUT OF REACH OF CHILDREN

If product is swallowed, get medical help or contact a Poison Control Center right away.

DIRECTIONS

• Apply as needed.

• After washing your face, take a suitable amount of the product and softly spread it on your face and neck to be absorbed.

INACTIVE INGREDIENTS

LEPIDIUM MEYENII ROOT EXTRACT, ASPARAGUS COCHINCHINENSIS ROOT EXTRACT, AUREOBASIDIUM PULLULANS FERMENT, DIPROPYLENE GLYCOL, GLYCERIN, NELUMBO NUCIFERA FLOWER EXTRACT, ORYZA SATIVA (RICE) EXTRACT, ARTEMISIA ANNUA EXTRACT, SACCHAROMYCES FERMENT, 1,2-HEXANEDIOL, GLYCYRRHIZA GLABRA (LICORICE) ROOT EXTRACT, CHAMAECYPARIS OBTUSA LEAF EXTRACT, CHRYSANTHELLUM INDICUM EXTRACT, COPTIS JAPONICA ROOT EXTRACT, CORYDALIS TURTSCHANINOVII ROOT EXTRACT, HOUTTUYNIA CORDATA EXTRACT, ILLICIUM VERUM (ANISE) FRUIT EXTRACT, LARIX SIBIRICA WOOD EXTRACT, LONICERA JAPONICA (HONEYSUCKLE) FLOWER EXTRACT, RHEUM PALMATUM ROOT/STALK EXTRACT, CETEARYL ETHYLHEXANOATE, BUTYLENE GLYCOL, SEA WATER, PENTAERYTHRITYL TETRAISOSTEARATE, ARGININE, CARBOMER 934, SCLEROTIUM GUM, CETEARYL OLIVATE, WATER, SORBITAN OLIVATE, SQUALANE, SODIUM PALMITOYL PROLINE, OLEA EUROPAEA (OLIVE) FRUIT OIL, ROSMARINUS OFFICINALIS (ROSEMARY) LEAF EXTRACT, ALOE BARBADENSIS LEAF EXTRACT, ARGANIA SPINOSA KERNEL OIL, LIMNANTHES ALBA (MEADOWFOAM) SEED OIL, MACADAMIA TERNIFOLIA SEED OIL, PORTULACA OLERACEA EXTRACT, PROPOLIS EXTRACT, PRUNUS PERSICA (PEACH) LEAF EXTRACT, PUNICA GRANATUM FRUIT EXTRACT, SALVIA OFFICINALIS (SAGE) LEAF EXTRACT, AVENA SATIVA (OAT) KERNEL EXTRACT, CENTELLA ASIATICA LEAF EXTRACT, CEREUS GRANDIFLORUS (CACTUS) EXTRACT, OCIMUM BASILICUM (BASIL) FLOWER/LEAF/STEM EXTRACT, SALVIA HISPANICA SEED EXTRACT, ETHYLHEXYLGLYCERIN, NYMPHAEA ALBA FLOWER EXTRACT, TOCOPHERYL ACETATE .ALPHA.-TOCOPHEROL ACETATE, CITRUS AURANTIUM DULCIS (ORANGE) PEEL OIL, DISODIUM EDTA, EUCALYPTUS GLOBULUS LEAF OIL, LAVANDULA ANGUSTIFOLIA (LAVENDER) OIL, LAVANDULA HYBRIDA OIL, OCTYLDODECANOL, ROSMARINUS OFFICINALIS (ROSEMARY) LEAF OIL, MELALEUCA ALTERNIFOLIA (TEA TREE) LEAF OIL, CENTELLA ASIATICA EXTRACT, CITRUS AURANTIFOLIA (LIME) OIL, POLYGONUM CUSPIDATUM ROOT EXTRACT, SCUTELLARIA BAICALENSIS ROOT EXTRACT, CAMELLIA SINENSIS LEAF EXTRACT, MORINGA PTERYGOSPERMA SEED EXTRACT, CHAMOMILLA RECUTITA (MATRICARIA) FLOWER EXTRACT

OTHER INFORMATION

Protect this product from excessive heat and direct sun.

QUESTIONS OR COMMENTS?

Call toll free 1-800-311-6680